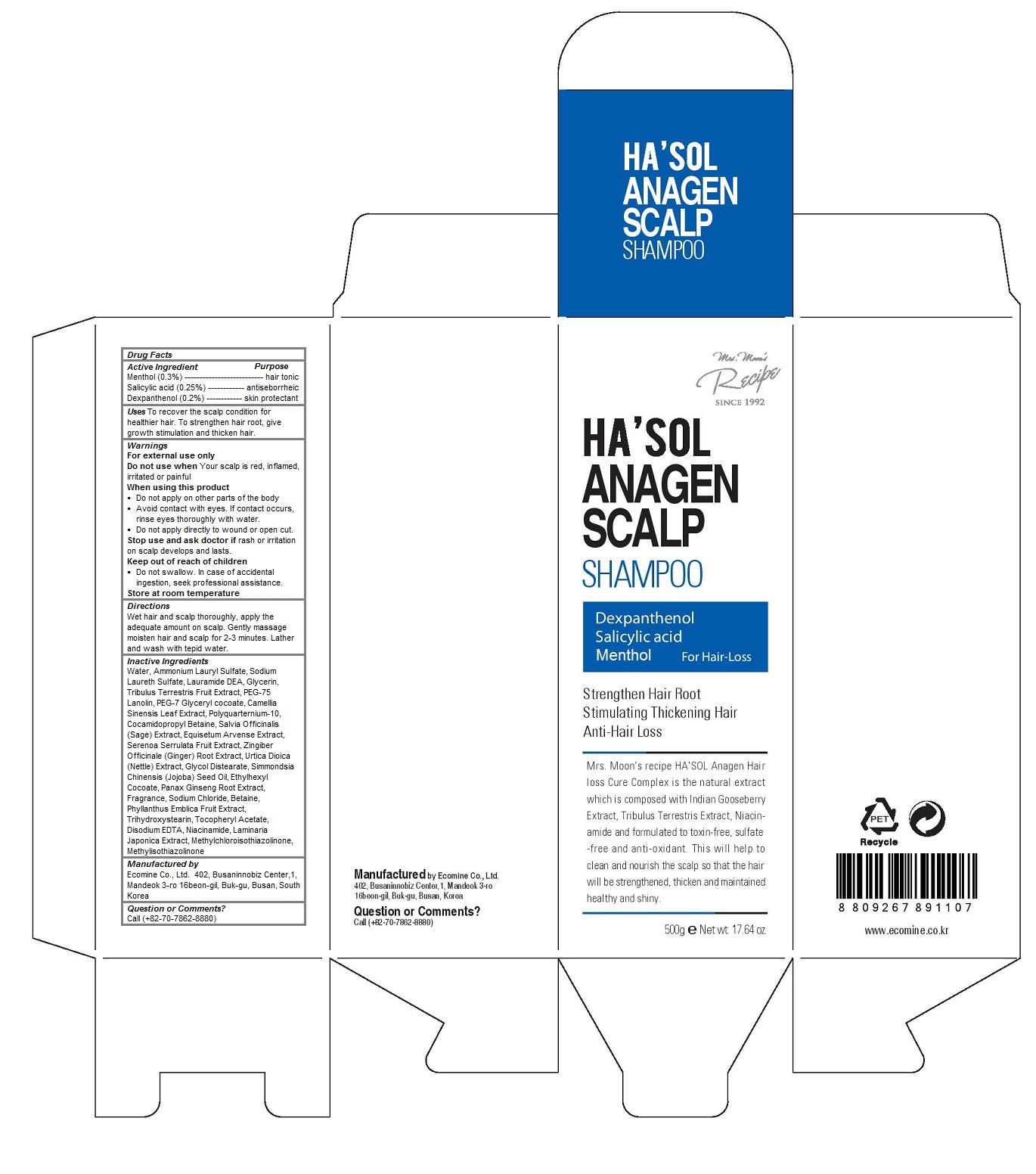 DRUG LABEL: HASOL Anagen Scalp
NDC: 51270-123 | Form: SHAMPOO
Manufacturer: ECOMINE Co., Ltd.
Category: otc | Type: HUMAN OTC DRUG LABEL
Date: 20160407

ACTIVE INGREDIENTS: Menthol 0.003 1/500 g; Salicylic Acid 0.0025 1/500 g; Dexpanthenol 0.002 1/500 g
INACTIVE INGREDIENTS: water; Ammonium Lauryl Sulfate; Sodium Laureth Sulfate; LAURIC DIETHANOLAMIDE; Glycerin; TRIBULUS TERRESTRIS FRUIT; PEG-75 LANOLIN; PEG-7 GLYCERYL COCOATE; GREEN TEA LEAF; COCAMIDOPROPYL BETAINE; SALVIA OFFICINALIS ROOT; EQUISETUM ARVENSE BRANCH; SAW PALMETTO; GINGER; URTICA DIOICA LEAF; Glycol Distearate; JOJOBA OIL; ETHYLHEXYL COCOATE; ASIAN GINSENG; Sodium Chloride; Betaine; PHYLLANTHUS EMBLICA FRUIT; Trihydroxystearin; .ALPHA.-TOCOPHEROL ACETATE; EDETATE DISODIUM; LAMINARIA JAPONICA; METHYLCHLOROISOTHIAZOLINONE; METHYLISOTHIAZOLINONE

HA'SOL Anagen Scalp Shampoo